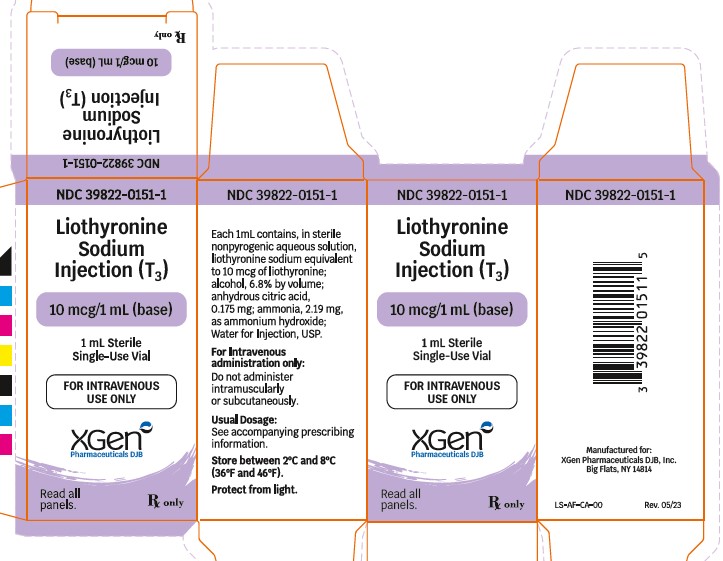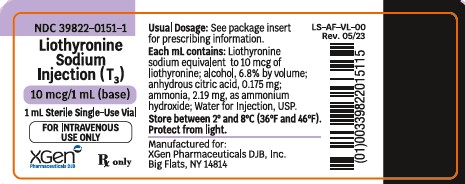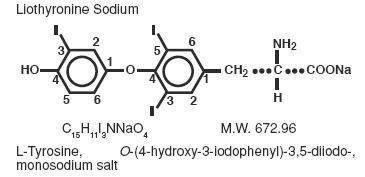 DRUG LABEL: Liothyronine Sodium
NDC: 39822-0151 | Form: INJECTION, SOLUTION
Manufacturer: XGen Pharmaceuticals DJB, Inc.
Category: prescription | Type: HUMAN PRESCRIPTION DRUG LABEL
Date: 20231201

ACTIVE INGREDIENTS: LIOTHYRONINE SODIUM 10 ug/1 mL
INACTIVE INGREDIENTS: ALCOHOL; ANHYDROUS CITRIC ACID; AMMONIA

LIOTHYRONINE SODIUM INJECTION (T3)
Rx Only

DESCRIPTION

Thyroid hormone drugs are natural or synthetic preparations containing tetraiodothyronine (T4, levothyroxine) sodium or triiodothyronine (T3, liothyronine) sodium or both. T4 and T3 are produced in the human thyroid gland by the iodination and coupling of the amino acid tyrosine. T4 contains four iodine atoms and is formed by the coupling of two molecules of diiodotyrosine (DIT). T3 contains three atoms of iodine and is formed by the coupling of one molecule of DIT with one molecule of monoiodotyrosine (MIT). Both hormones are stored in the thyroid colloid as thyroglobulin and released into the circulation. The major source of T3 has been shown to be peripheral deiodination of T4. T3 is bound less firmly than T4 in the serum, enters peripheral tissues more readily, and binds to specific nuclear receptor(s) to initiate hormonal, metabolic effects. T4 is the prohormone which is deiodinated to T3 for hormone activity.

Thyroid hormone preparations belong to two categories: (1) natural hormonal preparations derived from animal thyroid, and (2) synthetic preparations. Natural preparations include desiccated thyroid and thyroglobulin. Desiccated thyroid is derived from domesticated animals that are used for food by man (either beef or hog thyroid), and thyroglobulin is derived from thyroid glands of the hog.

Liothyronine sodium injection (T3) contains liothyronine (L-triiodothyronine or L-T3), a synthetic form of a natural thyroid hormone, as the sodium salt.

The structural and empirical formulas and molecular weight of liothyronine sodium are given below.

In euthyroid patients, 25 mcg of liothyronine is equivalent to approximately 1 grain of desiccated thyroid or thyroglobulin and 0.1 mg of L-thyroxine.

Each mL of liothyronine sodium injection (T3) in amber glass vials contains, in sterile non-pyrogenic aqueous solution, liothyronine sodium equivalent to 10 mcg of liothyronine; alcohol, 6.8% by volume; anhydrous citric acid, 0.175 mg; ammonia, 2.19 mg, as ammonium hydroxide; Water for Injection, USP.

CLINICAL PHARMACOLOGY

Thyroid hormones enhance oxygen consumption by most tissues of the body and increase the basal metabolic rate and the metabolism of carbohydrates, lipids and proteins. In vitro studies indicate that T3 increases aerobic mitochondrial function, thereby increasing the rates of synthesis and utilization of myocardial high-energy phosphates. This, in turn, stimulates myosin ATPase and reduces tissue lactic acidosis. Thus, thyroid hormones exert a profound influence on virtually every organ system in the body and are of particular importance in the development of the central nervous system.

While the source of levothyroxine (T4) and some triiodothyronine (T3) is via secretion from the thyroid gland, it is now well-established that approximately 80% of circulating T3 arises predominantly by way of the extrathyroidal conversion of T4. The membrane-bound enzyme responsible for this reaction is iodothyronine 5’-deiodinase. Activity of the enzyme is greatest in the liver and kidney. A second pathway of T4 to T3 conversion occurs via a PTU-insensitive 5’-deiodinase located primarily in the pituitary and central nervous system.

The prohormone T4 must be converted to T3 in the body before it can exert biological effects. During periods of illness or stress, this conversion is often inhibited and can be diverted to the inactive reverse T3 (rT3) moiety. Therefore, correction of the hypothyroid condition in patients with myxedema coma is facilitated by the parenteral administration of triiodothyronine (T3). T3 is bound much less firmly to serum binding proteins and therefore penetrates into the cells much more rapidly than T4. Also, the binding of T3 to a nuclear thyroid hormone receptor seems to initiate most effects of thyroid hormone in tissues. Although most thyroid hormone analogs, both natural and synthetic, will bind to this protein, the affinity of T3 for this receptor is roughly 10-fold higher than that of T4. Thus, T3 is the biologically active thyroid hormone.

Pharmacodynamics

The clinical features of myxedema coma include depression of the cardiovascular, respiratory, gastrointestinal and central nervous systems, impaired diuresis, and hypothermia. Administration of thyroid hormones reverses or attenuates these conditions. Thyroid hormones increase heart rate, ventricular contractility and cardiac output, as well as decrease total systemic vascular resistance. They also increase the rate and depth of respiration, motility of the gastrointestinal tract, rapidity of cerebration, and vasodilatation. Thyroid hormones correct hypothermia by markedly increasing the basal metabolic rate, as well as the number and activity of mitochondria in almost all cells of the body.

Pharmacokinetics

Since liothyronine sodium (T3) is not firmly bound to serum protein, it is readily available to body tissues.

Liothyronine sodium has a rapid cutoff of activity which permits quick dosage adjustment and facilitates control of the effects of overdosage, should they occur.

The higher affinity of levothyroxine (T4) as compared to triiodothyronine (T3) for both thyroid-binding globulin and thyroid-binding prealbumin partially explains the higher serum levels and longer half-life of the former hormone. Both protein-bound hormones exist in reverse equilibrium with minute amounts of free hormone, the latter accounting for the metabolic activity. T4 is deiodinated to T3.

A single dose of liothyronine sodium administered intravenously produces a detectable metabolic response in as little as two to four hours and a maximum therapeutic response within two days. However, no pharmacokinetic studies have been performed with intravenous liothyronine (T3) in myxedema coma or precoma patients.

INDICATIONS AND USAGE

Liothyronine sodium injection (T3) is indicated in the treatment of myxedema coma/precoma.

Liothyronine sodium injection (T3) can be used in patients allergic to desiccated thyroid or thyroid extract derived from pork or beef.

CONTRAINDICATIONS

Thyroid hormone preparations are generally contraindicated in patients with diagnosed but as yet uncorrected adrenal cortical insufficiency or untreated thyrotoxicosis. Thyroid hormone preparations are also generally contraindicated in patients with hypersensitivity to any of the active or extraneous constituents of these preparations; however, there is no well-documented evidence in the literature of true allergic or idiosyncratic reactions to thyroid hormone.

Concomitant use of liothyronine sodium injection (T3) and artificial rewarming of patients is contraindicated. (See PRECAUTIONS.)

BOXED WARNING

Drugs with thyroid hormone activity, alone or together with other therapeutic agents, have been used for the treatment of obesity. In euthyroid patients, doses within the range of daily hormonal requirements are ineffective for weight reduction. Larger doses may produce serious or even life-threatening manifestations of toxicity, particularly when given in association with sympathomimetic amines such as those used for their anorectic effects.

WARNINGS

The use of thyroid hormones in the therapy of obesity, alone or combined with other drugs, is unjustified and has been shown to be ineffective. Neither is their use justified for the treatment of male or female infertility unless this condition is accompanied by hypothyroidism.

Thyroid hormones should be used with great caution in a number of circumstances where the integrity of the cardiovascular system, particularly the coronary arteries, is suspect. These include patients with angina pectoris or the elderly, in whom there is a greater likelihood of occult cardiac disease. Therefore, in patients with compromised cardiac function, use thyroid hormones in conjunction with careful cardiac monitoring. Although the specific dosage of liothyronine sodium injection (T3) depends upon individual circumstances, in patients with known or suspected cardiovascular disease the extremely rapid onset of action of liothyronine sodium injection (T3) may warrant initiating therapy at a dose of 10 mcg to 20 mcg. (See DOSAGE AND ADMINISTRATION.)

Myxedematous patients are very sensitive to thyroid hormones; dosage should be started at a low level and increased gradually as acute changes may precipitate adverse cardiovascular events.

Severe and prolonged hypothyroidism can lead to a decreased level of adrenocortical activity commensurate with the lowered metabolic state. When thyroid replacement therapy is administered, the metabolism increases at a greater rate than adrenocortical activity. This can precipitate adrenocortical insufficiency. Therefore, in severe and prolonged hypothyroidism, supplemental adrenocortical steroids may be necessary.

In rare instances, the administration of thyroid hormone may precipitate a hyperthyroid state or may aggravate existing hyperthyroidism.

Extreme caution is advised when administering thyroid hormones with digitalis or vasopressors. (See PRECAUTIONS-Drug Interactions.)

Fluid therapy should be administered with great care to prevent cardiac decompensation. (See PRECAUTIONS-Adjunctive Therapy.)

PRECAUTIONS

General

Thyroid hormone therapy in patients with concomitant diabetes mellitus (see PRECAUTIONS-Drug Interactions, Insulin or Oral Hypoglycemics regarding interaction and dose adjustment with insulin) or insipidus or adrenal cortical insufficiency may aggravate the intensity of their symptoms. Appropriate adjustments of the various therapeutic measures directed at these concomitant endocrine diseases are required.

The therapy of myxedema coma requires simultaneous administration of glucocorticoids. (See PRECAUTIONS-Adjunctive Therapy).

Hypothyroidism decreases and hyperthyroidism increases the sensitivity to anticoagulants. Prothrombin time should be closely monitored in thyroid-treated patients on anticoagulants and dosage of the latter agents adjusted on the basis of frequent prothrombin time determinations.

Oral therapy should be resumed as soon as the clinical situation has been stabilized and the patient is able to take oral medication. If L-thyroxine rather than liothyronine sodium is used in initiating oral therapy, the physician should bear in mind that there is a delay of several days in the onset of L-thyroxine activity and that intravenous therapy should be discontinued gradually.

Adjunctive Therapy

Many investigators recommend that corticosteroids be administered routinely in the initial emergency treatment of all patients with myxedema coma. Patients with pituitary myxedema should receive adrenocortical hormone replacement therapy at or before the start of liothyronine sodium injection (T3) therapy. Similarly, patients with primary myxedema may also require adrenocortical hormone replacement therapy since a rapid return to normal body metabolism from a severely hypothyroid state may result in acute adrenocortical insufficiency and shock.

In considering the need to elevate blood pressure, it should be kept in mind that tissue metabolic requirements are markedly reduced in the hypothyroid patient. Because arrhythmias and circulatory collapse have infrequently occurred following the concomitant administration of thyroid hormones and vasopressor therapies, use caution when administering these therapies concomitantly. (See PRECAUTIONS-Drug Interactions, Vasopressors.)

Hyponatremia is frequently present in myxedema coma, but usually resolves without specific therapy as the metabolic status of the patient is improved with thyroid hormone treatment. Fluid therapy should be administered with great care to prevent cardiac decompensation. In addition, some patients with myxedema have inappropriate secretion of ADH and are susceptible to water intoxication.

In some patients, respiratory depression has been a significant factor in the development or persistence of the comatose state. Decreased oxygen saturation and elevated CO2 levels respond quickly to artificial respiration.

Infection is often present in myxedema coma and should be looked for and treated appropriately.

Concomitant use of liothyronine sodium injection (T3) and artificial rewarming of patients is contraindicated. Although patients in myxedema coma are often hypothermic, most investigators believe that artificial rewarming is of little value or may be harmful. The peripheral vasodilation produced by external heat serves to further decrease circulation to vital internal organs and to increase shock if present. It has been reported that the administration of liothyronine sodium will restore a normal body temperature in 24 to 48 hours if heat loss is prevented by keeping the patient covered with blankets in a warm room.

Laboratory Tests

Treatment of patients with thyroid hormones requires the periodic assessment of thyroid status by means of appropriate laboratory tests besides the full clinical evaluation. Serum T3 and TSH levels should be monitored to assess dosage adequacy and biologic effectiveness.

Drug Interactions

Oral Anticoagulants: Thyroid hormones appear to increase catabolism of vitamin K-dependent clotting factors. If oral anticoagulants are also being given, compensatory increases in clotting factor synthesis are impaired. Patients stabilized on oral anticoagulants who are found to require thyroid replacement therapy should be watched very closely when thyroid is started. If a patient is truly hypothyroid, it is likely that a reduction in anticoagulant dosage will be required. No special precautions appear to be necessary when oral anticoagulant therapy is begun in a patient already stabilized on maintenance thyroid replacement therapy.

Insulin or Oral Hypoglycemics:Initiating thyroid replacement therapy may cause increases in insulin or oral hypoglycemic requirements. The effects seen are poorly understood and depend upon a variety of factors such as dose and type of thyroid preparations and endocrine status of the patient. Patients receiving insulin or oral hypoglycemics should be closely watched during initiation of thyroid replacement therapy.

Estrogen, Oral Contraceptives:Estrogens tend to increase serum thyroxine-binding globulin (TBG). In a patient with a nonfunctioning thyroid gland who is receiving thyroid replacement therapy, free levothyroxine may be decreased when estrogens are started thus increasing thyroid requirements. However, if the patient’s thyroid gland has sufficient function, the decreased free thyroxine will result in a compensatory increase in thyroxine output by the thyroid. Therefore, patients without a functioning thyroid gland who are on thyroid replacement therapy may need to increase their thyroid dose if estrogens or estrogen-containing oral contraceptives are given.

Tricyclic Antidepressants:Use of thyroid products with imipramine and other tricyclic antidepressants may increase receptor sensitivity and enhance antidepressant activity; transient cardiac arrhythmias have been observed. Thyroid hormone activity may also be enhanced.

Digitalis:Thyroid preparations may potentiate the toxic effects of digitalis. Thyroid hormonal replacement increases metabolic rate, which requires an increase in digitalis dosage.

Ketamine:When administered to patients on a thyroid preparation, this parenteral anesthetic may cause hypertension and tachycardia. Use with caution and be prepared to treat hypertension, if necessary.

Vasopressors:Thyroid hormones increase the adrenergic effect of catecholamines such as epinephrine and norepinephrine. Therefore, use of vasopressors in patients receiving thyroid hormone preparations may increase the risk of precipitating coronary insufficiency, especially in patients with coronary artery disease. Therefore, use caution when administering vasopressors with liothyronine (T3).

DRUG/LABORATORY TEST INTERACTIONS

The following drugs or moieties are known to interfere with laboratory tests performed in patients on thyroid hormone therapy: androgens, corticosteroids, estrogens, oral contraceptives containing estrogens, iodine-containing preparations and the numerous preparations containing salicylates.

1. Changes in TBG concentration should be taken into consideration in the interpretation of T4 and T3 values. In such cases, the unbound (free) hormone should be measured. Pregnancy, estrogens and estrogen-containing oral contraceptives increase TBG concentrations. TBG may also be increased during infectious hepatitis. Decreases in TBG concentrations are observed in nephrosis, acromegaly and after androgen or corticosteroid therapy. Familial hyper- or hypothyroxine-binding globulinemias have been described. The incidence of TBG deficiency approximates 1 in 9000. The binding of thyroxine by thyroxine-binding prealbumin (TBPA) is inhibited by salicylates.
2. Medicinal or dietary iodine interferes with all in vivo tests of radioiodine uptake, producing low uptakes which may not be reflective of a true decrease in hormone synthesis.

Carcinogenesis, Mutagenesis, Impairment of Fertility

A reportedly apparent association between prolonged thyroid therapy and breast cancer has not been confirmed and patients on thyroid for established indications should not discontinue therapy. No confirmatory long-term studies in animals have been performed to evaluate carcinogenic potential, mutagenicity, or impairment of fertility in either males or females.

Pregnancy

Pregnancy Category A: Thyroid hormones do not readily cross the placental barrier. The clinical experience to date does not indicate any adverse effect on fetuses when thyroid hormones are administered to pregnant women. On the basis of current knowledge, thyroid replacement therapy to hypothyroid women should not be discontinued during pregnancy.

Nursing Mothers

Minimal amounts of thyroid hormones are excreted in human milk. Thyroid hormones are not associated with serious adverse reactions and do not have a known tumorigenic potential. However, caution should be exercised when thyroid hormones are administered to a nursing woman.

Geriatric Use

Clinical studies of liothyronine sodium did not include sufficient numbers of subjects aged 65 and over to determine whether they respond differently from younger subjects. Other reported clinical experience has not identified differences in responses between the elderly and younger patients. In general, dose selection for an elderly patient should be cautious, usually starting at the low end of the dosing range, reflecting the greater frequency of decreased hepatic, renal, or cardiac function, and of concomitant disease or other drug therapy. This drug is known to be substantially excreted by the kidney, and the risk of toxic reactions to this drug may be greater in patients with impaired renal function. Because elderly patients are more likely to have decreased renal function, care should be taken in dose selection, and it may be useful to monitor renal function.

Pediatric Use

There is limited experience with liothyronine sodium injection (T3) in the pediatric population. Safety and effectiveness in pediatric patients have not been established.

ADVERSE REACTIONS

The most frequently reported adverse events were arrhythmia (6% of patients) and tachycardia (3%). Cardiopulmonary arrest, hypotension and myocardial infarction occurred in approximately 2% of patients. The following events occurred in approximately 1% or fewer of patients: angina, congestive heart failure, fever, hypertension, phlebitis and twitching.

In rare instances, allergic skin reactions have been reported with liothyronine sodium tablets.

OVERDOSAGE

Signs and Symptoms:Headache, irritability, nervousness, tremor, sweating, increased bowel motility and menstrual irregularities. Angina pectoris, arrhythmia, tachycardia, acute myocardial infarction or congestive heart failure may be induced or aggravated. Shock may also develop if there is untreated pituitary or adrenocortical failure. Massive overdosage may result in symptoms resembling thyroid storm.

Treatment of Overdosage:Dosage should be reduced or therapy temporarily discontinued if signs and symptoms of overdosage appear. Treatment may be reinstituted at a lower dosage. In normal individuals, normal hypothalamic-pituitary- thyroid axis function is restored in six to eight weeks after cessation of therapy following thyroid suppression.

Treatment is symptomatic and supportive. Oxygen may be administered and ventilation maintained. Cardiac glycosides may be indicated if congestive heart failure develops. Beta-adrenergic antagonists have been used advantageously in the treatment of increased sympathetic activity. Measures to control fever, hypoglycemia or fluid loss should be instituted if needed.

DOSAGE AND ADMINISTRATION

Adults
Myxedema coma is usually precipitated in the hypothyroid patient of long standing by intercurrent illness or drugs such as sedatives and anesthetics and should be considered a medical emergency. Therapy should be directed at the correction of electrolyte disturbances, possible infection, or other intercurrent illness in addition to the administration of intravenous liothyronine (T3). Simultaneous glucocorticosteroids are required.

Liothyronine sodium injection (T3) is for intravenous administration only. It should not be given intramuscularly or subcutaneously.

Prompt administration of an adequate dose of intravenous liothyronine (T3) is important in determining clinical outcome.
Initial and subsequent doses of liothyronine sodium injection (T3) should be based on continuous monitoring of the patient’s clinical status and response to therapy.
Liothyronine sodium injection (T3) should normally be administered at least four hours-and not more than 12 hours-apart.
Administration of at least 65 mcg/day of intravenous liothyronine (T3) in the initial days of therapy was associated with lower mortality.
There is limited clinical experience with intravenous liothyronine (T3) at total daily doses exceeding 100 mcg/day.

No controlled clinical studies have been done with liothyronine sodium injection (T3). The following dosing guidelines have been derived from data analysis of myxedema coma/precoma case reports collected by SmithKline Beecham Pharmaceuticals since 1963 and from scientific literature since 1956.

An initial intravenous liothyronine sodium injection (T3) dose ranging from 25 mcg to 50 mcg is recommended in the emergency treatment of myxedema coma/precoma in adults. In patients with known or suspected cardiovascular disease, an initial dose of 10 mcg to 20 mcg is suggested (see WARNINGS). However, both the initial dose and subsequent doses should be determined on the basis of continuous monitoring of the patient’s clinical condition and response to liothyronine sodium injection (T3) therapy. Normally at least four hours should be allowed between doses to adequately assess therapeutic response and no more than 12 hours should elapse between doses to avoid fluctuations in hormone levels. Caution should be exercised in adjusting the dose due to the potential of large changes to precipitate adverse cardiovascular events. Review of the myxedema case reports indicates decreased mortality in patients receiving at least 65 mcg/day in the initial days of treatment. However, there is limited clinical experience at total daily doses above 100 mcg. See PRECAUTIONS-Drug Interactions for potential interactions between thyroid hormones and digitalis and vasopressors.

Pediatric Use
There is limited experience with liothyronine sodium injection (T3) in the pediatric population. Safety and effectiveness in pediatric patients have not been established.

Switching to Oral Therapy
Oral therapy should be resumed as soon as the clinical situation has been stabilized and the patient is able to take oral medication. When switching a patient to liothyronine sodium tablets from liothyronine sodium injection (T3), discontinue liothyronine sodium injection (T3), initiate oral therapy at a low dosage, and increase gradually according to the patient’s response.

If L-thyroxine rather then liothyronine sodium is used in initiating oral therapy, the physician should bear in mind that there is a delay of several days in the onset of L-thyroxine activity and that intravenous therapy should be discontinued gradually.

HOW SUPPLIED

Liothyronine sodium injection (T3) is supplied in a single vial carton containing a 1mL vial at a concentration of 10 mcg/1mL (base). NDC number 39822-0151-1.

Storage and Handling

Store between 2°C – 8°C (36°F – 46°F).

Manufactured for:

XGen Pharmaceuticals DJB, Inc.
Big Flats, NY 14814

Revised: May 2023
LS-AF-PI-00

PACKAGE LABEL.PRINCIPAL DISPLAY PANEL

NDC 39822-0151-1
Liothyronine Injection
10 mcg/1mL (Base activity)
For Intravenous Use
Rx Only
1 Vial
XGen Pharmaceuticals DJB, Inc.

NDC 39822-0151-1
Liothyronine Injection
10 mcg/1mL (Base activity)
For Intravenous Use
Rx Only
1 Vial
XGen Pharmaceuticals DJB, Inc.